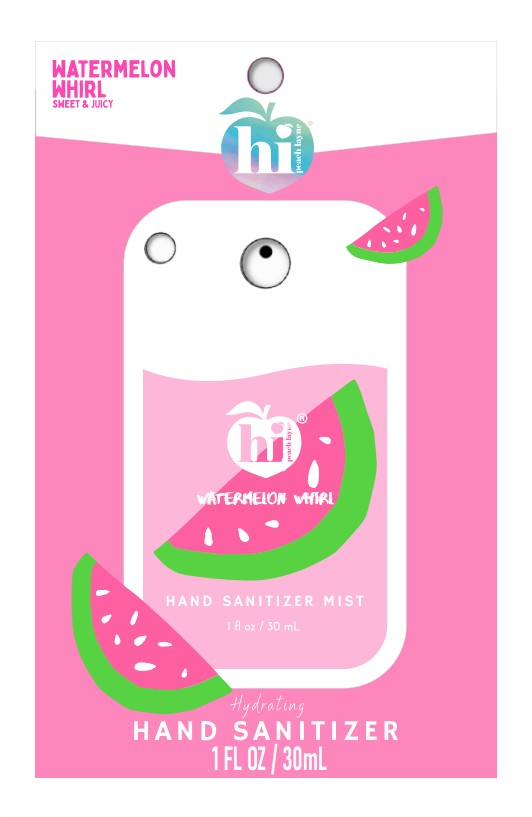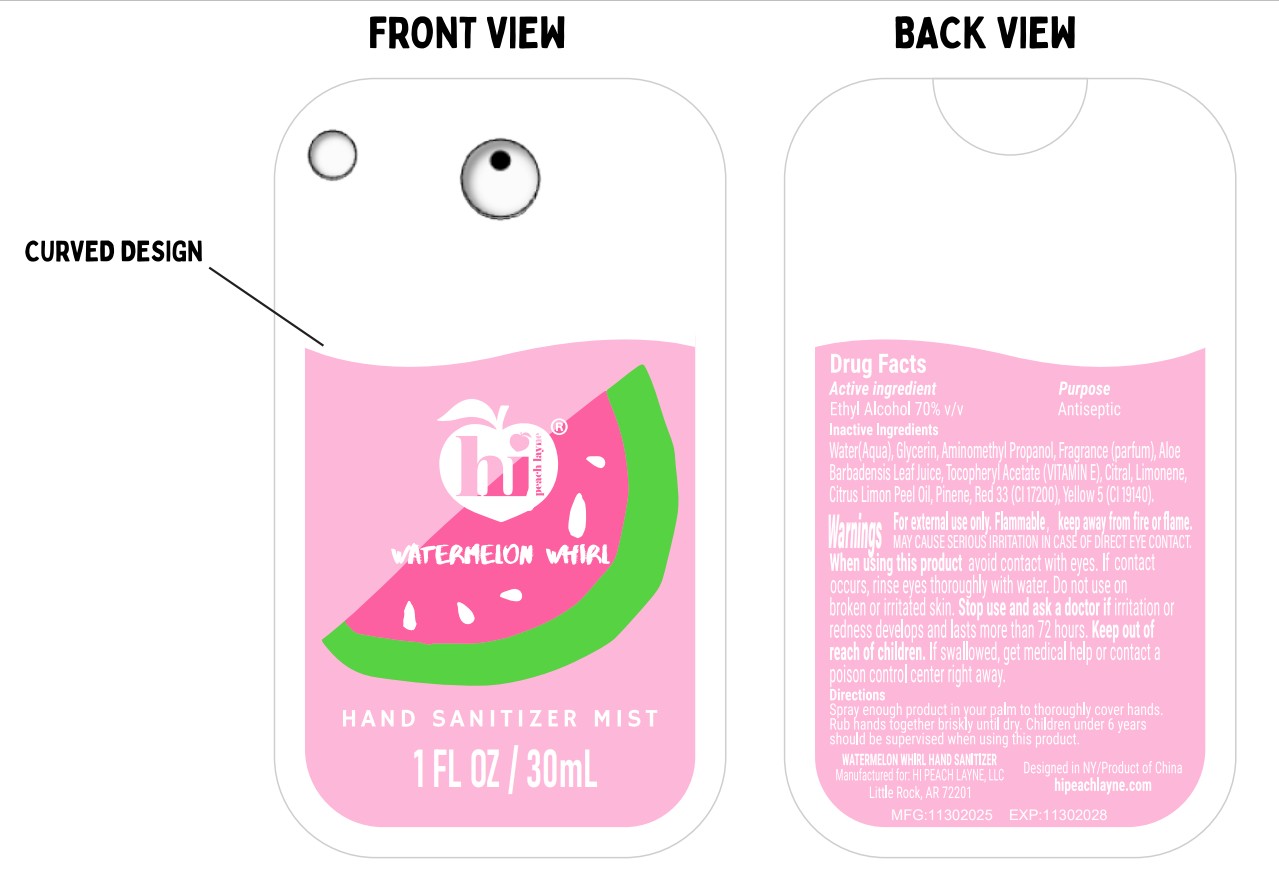 DRUG LABEL: hi peach layne
NDC: 73905-050 | Form: SPRAY
Manufacturer: Zhejiang Jinghui Cosmetics Share Co., Ltd.
Category: otc | Type: HUMAN OTC DRUG LABEL
Date: 20260116

ACTIVE INGREDIENTS: ALCOHOL 70 mL/100 mL
INACTIVE INGREDIENTS: ALOE BARBADENSIS LEAF JUICE; LIMONENE, (+)-; GLYCERIN; ALPHA-TOCOPHEROL ACETATE; YELLOW 5; CITRAL; RED 33; LEMON OIL, COLD PRESSED; FRAGRANCE 13576; WATER; PINENE; AMINOMETHYL PROPANOL

4-WATERMELON WHIRL HAND SANITIZER-73095-050-30ml

ACTIVE INGREDIENT

Ethyl Alcohol 70% v/v

PURPOSE

Antiseptic

INACTIVE INGREDIENT

Water(Aqua), Glycerin, Aminomethyl Propanol, Fragrance (parfum), Aloe Barbadensis Leaf Juice, Tocopheryl Acetate (VITAMIN E), Citral, Limonene, Citrus Limon Peel 0il, Pinene, Red 33 (CI 17200), Yellow 5(Cl 19140)

WARNINGS

For external use only. Flammable, keep away from fire or flame.

MAY CAUSE SERIOUS IRRITATION IN CASE OF DIRECT EYE CONTACT. When using this product avoid contact with eyes. If contact occurs, rinse eyes thoroughly with water. Do not use on broken or irritated skin. Stop use and ask a doctor if irritation or redness develops and lasts more than 72 hours.

Keep out of reach of children. If swallowed, get medical help or contact a poison control center right away.

INDICATIONS AND USAGE

Spray enough product in your palm to thoroughly cover hands. Rub hands together briskly until dry. Children under 6 years should be supervised when using this product.

DOSAGE AND ADMINISTRATION

Spray enough product in your palm to thoroughly cover hands. Rub hands together briskly until dry.